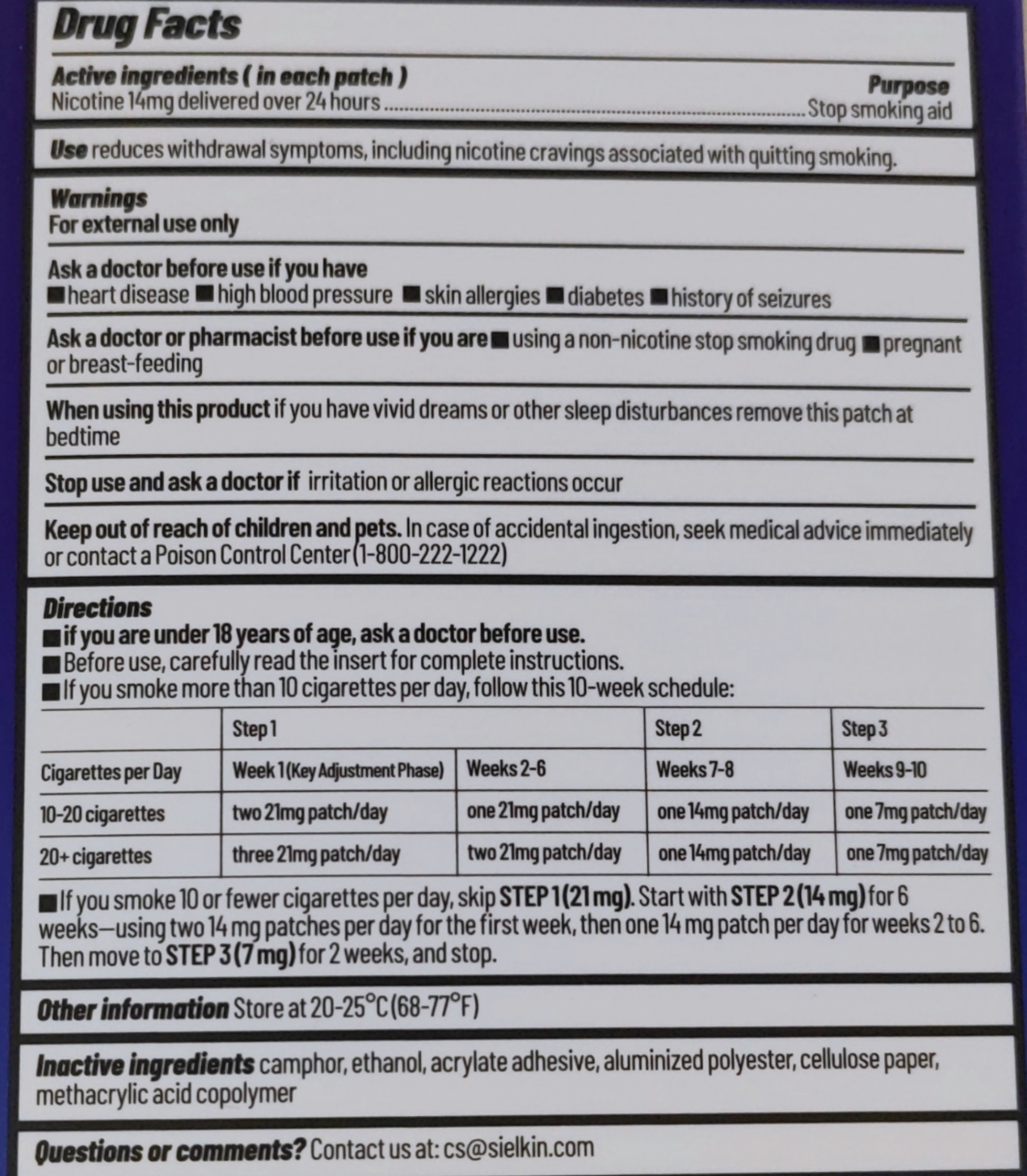 DRUG LABEL: Sielkin QUIT SMOKING NICOTINE PATCHES 14mg
NDC: 83364-016 | Form: PATCH
Manufacturer: YITONGBADA (SHENZHEN) INTERNATIONAL TRADE CO., LTD
Category: otc | Type: HUMAN OTC DRUG LABEL
Date: 20260128

ACTIVE INGREDIENTS: NICOTINE 14 mg/1 g
INACTIVE INGREDIENTS: ACRYLIC ACID; METHACRYLIC ACID - METHYL METHACRYLATE COPOLYMER (1:1); BORNEOL; ALCOHOL

Sielkin QUIT SMOKING NICOTINE PATCHES 14mg

Drug Facts

Active ingredients (in each patch)
Nicotine 14mg delivered over 24 hours

PURPOSE

Stop smoking aid

INDICATIONS AND USAGE

reduces withdrawal symptoms, including nicotine cravings associated with quitting smoking.

Ask a doctor before use if you have
■heart disease ■high blood pressure ■skin allergies ■diabetes ■history of seizures

Ask a doctor or pharmacist before use if you are■using a non-nicotine stop smoking drug■pregnant or breast-feeding

When using this product
if you have vivid dreams or other sleep disturbances remove this patch at bedtime.

Stop use and ask a doctor if irritation or allergic reactions occur

Keep out of reach of children and pets. In case of accidental ingestion, seek medical advice immediately or contact a Poison Control Center(1-800-222-1222)

Warnings

For external use only

Directions
■if you are under 18 years of age, ask a doctor before use.
■Before use, carefuly read the insert for complete instructions.
■lf you smoke more than 10 cigarettes per day, follow this 10-week schedule:

 | Step 1 |  | Step 2 | Step 3
Cigarettes per Day | Week 1(Key Adjustment Phase) | Weeks 2-6 | Weeks 7-8 | Weeks 9-10
10-20 cigarettes | two 21mg patch/day | one 21mg patch/day | one 14mg patch/day | one 7 mg patch/day
20+ cigarettes | three 21mg patch/day | two 21mg patch/day | one 14mg patch/day | one 7 mg patch/day

■lf you smoke 10 or fewer cigarettes per day, skip STEP 1(21mg). Start with STEP 2(14mg) for 6 weeks-using two14mg patches per day for the first week, then one 14mg patch per day for weeks 2 to 6. Then move to STEP 3(7mg) for 2weeks, and stop.

Other information Store at 20-25℃ (68-77°F)

INACTIVE INGREDIENT

Inactive ingredients camphor, ethanol, acrylate adhesive, aluminized polyester, cellulose paper, methacrylic acid copolymer